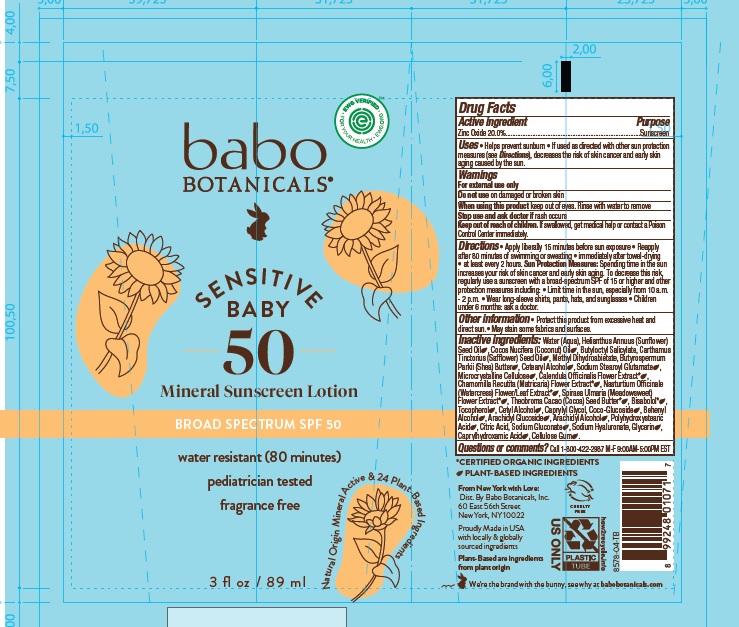 DRUG LABEL: Babo Botanicals Sensitive Baby Mineral Sunscreen SPF50
NDC: 79265-8758 | Form: LOTION
Manufacturer: Babo Botanicals, Inc.
Category: otc | Type: HUMAN OTC DRUG LABEL
Date: 20250130

ACTIVE INGREDIENTS: ZINC OXIDE 200 mg/1 mL
INACTIVE INGREDIENTS: CALENDULA OFFICINALIS FLOWER; CETOSTEARYL ALCOHOL; HYALURONATE SODIUM; SODIUM STEAROYL GLUTAMATE; TOCOPHEROL; LEVOMENOL; GLYCERIN; WATER; NASTURTIUM OFFICINALE FLOWERING TOP; POLYHYDROXYSTEARIC ACID (2300 MW); SODIUM GLUCONATE; CETYL ALCOHOL; CITRIC ACID MONOHYDRATE; CAPRYLYL GLYCOL; CARBOXYMETHYLCELLULOSE SODIUM, UNSPECIFIED FORM; CHAMOMILE; BUTYLOCTYL SALICYLATE; ARACHIDYL ALCOHOL; ARACHIDYL GLUCOSIDE; DOCOSANOL; SHEA BUTTER; CAPRYLHYDROXAMIC ACID; METHYL DIHYDROABIETATE; COCO GLUCOSIDE; COCONUT OIL; SUNFLOWER OIL; MICROCRYSTALLINE CELLULOSE; FILIPENDULA ULMARIA FLOWER; COCOA BUTTER; SAFFLOWER OIL

Babo Botanicals Sensitive Baby Mineral Sunscreen SPF50

Active ingredient

Zinc Oxide 20.0%

Purpose

Sunscreen

Uses

- Helps prevent sunburn.
- If used as directed with other sun protection measures (see Directions), decreases the risk of skin cancer and early skin aging caused by the sun.

Warnings

For external use only.

Do not use

on damaged or broken skin

When using this product

keep out of eyes. Rinse with water to remove

Stop use and ask doctor if

rash occurs

Keep out of reach of children.

If swallowed, get medical help or contact a Poison Control Center immediately.

Directions

- Apply liberally 15 minutes before sun exposure.
- Reapply after 80 minutes of swimming or sweating
- immediately after towel-drying
- at least every 2 hours.

Sun Protection Measures: Spending time in the sun increases your risk of skin cancer and early skin aging. To decrease this risk, regularly use a sunscreen with a broad-spectrum SPF of 15 or higher and other protection measures including:

- Limit time in the sun, especially from 10 a.m. - 2 p.m.
- Wear long-sleeve shirts, pants, hats, and sunglasses
- Children under 6 months: ask a doctor.

Other information

- Protect this product from excessive heat and direct sun
- May stain some fabrics and surfaces.

Inactive ingredients

Water (Aqua), Helianthus Annuus (Sunflower) Seed Oil, Cocos Nucifera (Coconut) Oil, Butyloctyl Salicylate, Carthamus Tinctorius (Safflower) Seed Oil, Methyl Dihydroabietate, Butyrospermum Parkii (Shea) Butter, Cetearyl Alcohol, Sodium Stearoyl Glutamate, Microcrystalline Cellulose, Calendula Officinalis Flower Extract*, Chamomilla Recutita (Matricaria) Flower Extract*, Nasturtium Officinale (Watercress) Flower/Leaf Extract*, Spiraea Ulmaria (Meadowsweet) Flower Extract*, Theobroma Cacao (Cocoa) Seed Butter*, Bisabolol*, Tocopherol, Cetyl Alcohol, Caprylyl Glycol, Coco-Glucoside, Behenyl Alcohol, Arachidyl Glucoside, Arachidyl Alcohol, Polyhydroxystearic Acid, Citric Acid, Sodium Gluconate, Sodium Hyaluronate, Glycerin, Caprylhydroxamic Acid, Cellulose Gum..*Certified Organic Ingredients

Questions or comments?

Call 1-800-422-2987 M-F 9:00AM-5:00PM EST